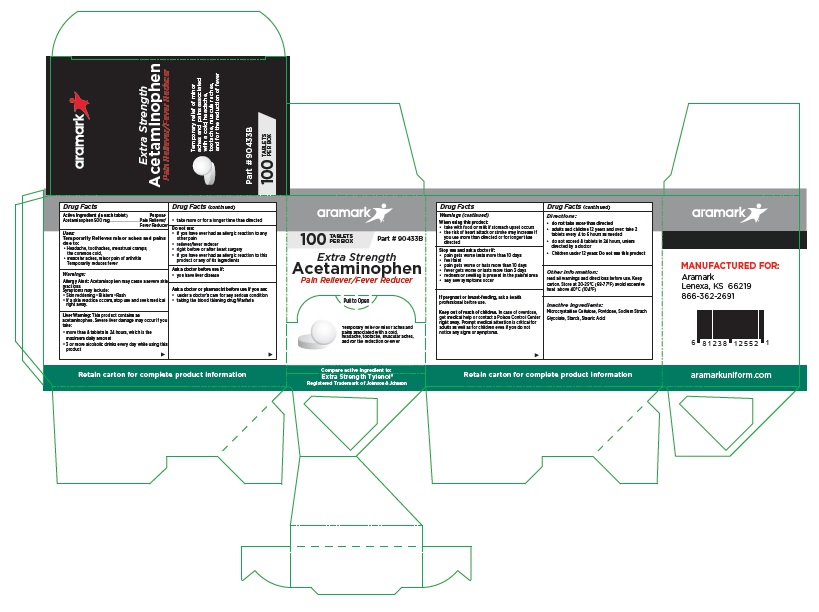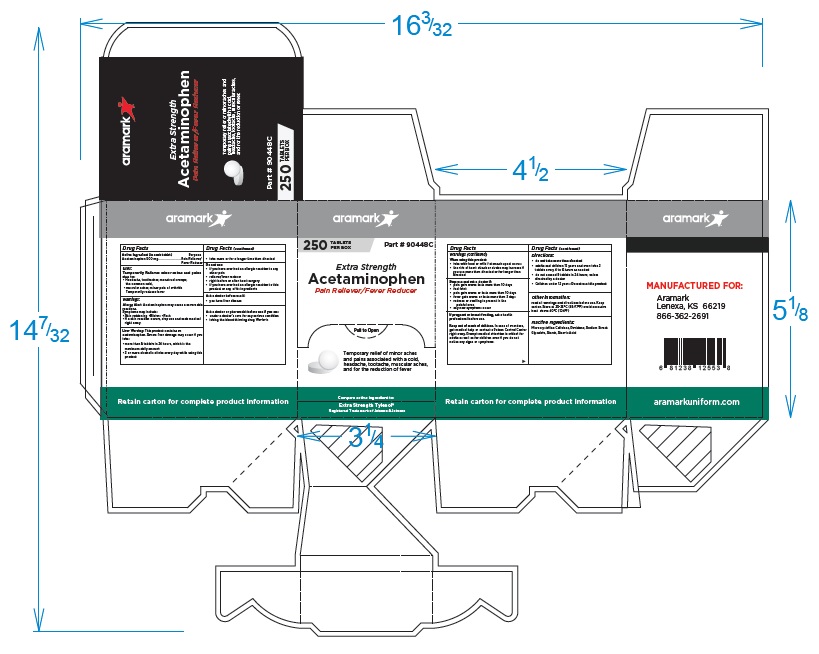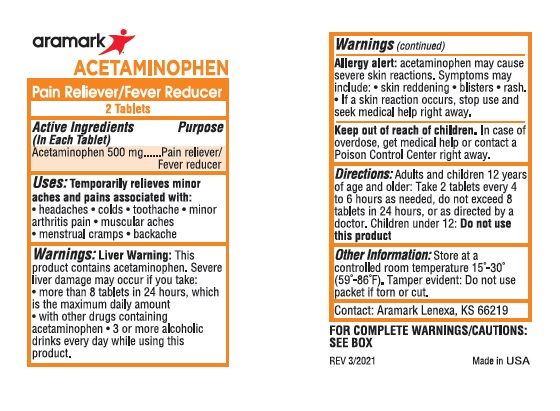 DRUG LABEL: Aramark Extra Strength Acetaminophen
NDC: 81238-3500 | Form: TABLET
Manufacturer: Western First Aid Safety DBA Aramark
Category: otc | Type: HUMAN OTC DRUG LABEL
Date: 20210719

ACTIVE INGREDIENTS: ACETAMINOPHEN 500 mg/1 1
INACTIVE INGREDIENTS: MICROCRYSTALLINE CELLULOSE; POVIDONE; SODIUM STARCH GLYCOLATE TYPE A CORN; STARCH, CORN; STEARIC ACID

Aramark Extra Strength Acetaminophen

Drug Facts

Active Ingredient (in each tablet)
Acetaminophen 500 mg

Purpose
Acetaminophen ...................Pain Reliever/Fever Reducer

Uses:
Temporarily Relieves minor aches and pains
due to:
• Headache, toothaches, menstrual cramps,
the common cold,
• muscular aches, minor pain of arthritis
Temporarily reduces fever

Warnings:
Allergy Alert: Acetaminophen may cause a severe skin
reactions.
Symptoms may include:
• Skin reddening •Blisters •Rash
• If a skin reaction occurs, stop use and seek medical
right away.

Liver Warning: This product contains an
acetaminophen. Severe liver damage may occur if you
take:
• more than 8 tablets in 24 hours, which is the
maximum daily amount
• 3 or more alcoholic drinks every day while using this
product

• take more or for a longer time than directed

Do not use:
• if you have ever had an allergic reaction to any
other pain
• reliever/fever reducer
• right before or after heart surgery
• if you have ever had an allergic reaction to this
product or any of its ingredients

Ask a doctor before use if:
• you have liver disease

Ask a doctor or pharmacist before use if you are:
• under a doctor’s care for any serious condition
• taking the blood thinning drug Warfarin

When using this product:
• take with food or milk if stomach upset occurs
• the risk of heart attack or stroke may increase if
you use more than directed or for longer than
directed

Stop use and ask a doctor if:
• pain gets worse lasts more than 10 days
• feel faint
• pain gets worse or lasts more than 10 days
• fever gets worse or lasts more than 3 days
• redness or swelling is present in the painful area
• any new symptoms occur

If pregnant or breast-feeding, ask a health
professional before use.

Keep out of reach of children. In case of overdose,
get medical help or contact a Poison Control Center
right away. Prompt medical attention is critical for
adults as well as for children even if you do not
notice any signs or symptoms.

Directions:
• do not take more than directed
• adults and children 12 years and over: take 2
tablets every 4 to 6 hours as needed
• do not exceed 8 tablets in 24 hours, unless
directed by a doctor
• Children under 12 years: Do not use this product

Other information:
read all warnings and directions before use. Keep
carton. Store at 20-25°C (68-77°F) avoid excessive
heat above 40°C (104°F)

Inactive Ingredients:
Microcrystalline Cellulose, Povidone, Sodium Starch
Glycolate, Starch, Stearic Acid

Package Labeling

aramark

100 TABLETS Part # 90433B
PER BOX

Extra Strength
Acetaminophen
Pain Reliever/Fever Reducer

Temporary relief of minor aches and
pains associated with a cold,
headache, tootache, muscular aches,
and for the reduction of fever

Compare active ingredient to:
Extra Strength Tylenol®
Registered Trademark of Johnson & Johnson

MANUFACTURED FOR:

Aramark
Lenexa, KS 66219
866-362-2691

aramarkuniform.com

Retain carton for complete product information

100 Tablet Box

250 Tablet Box

2-Tablet Packet

res